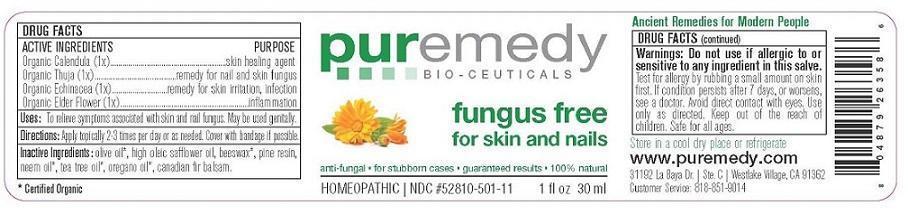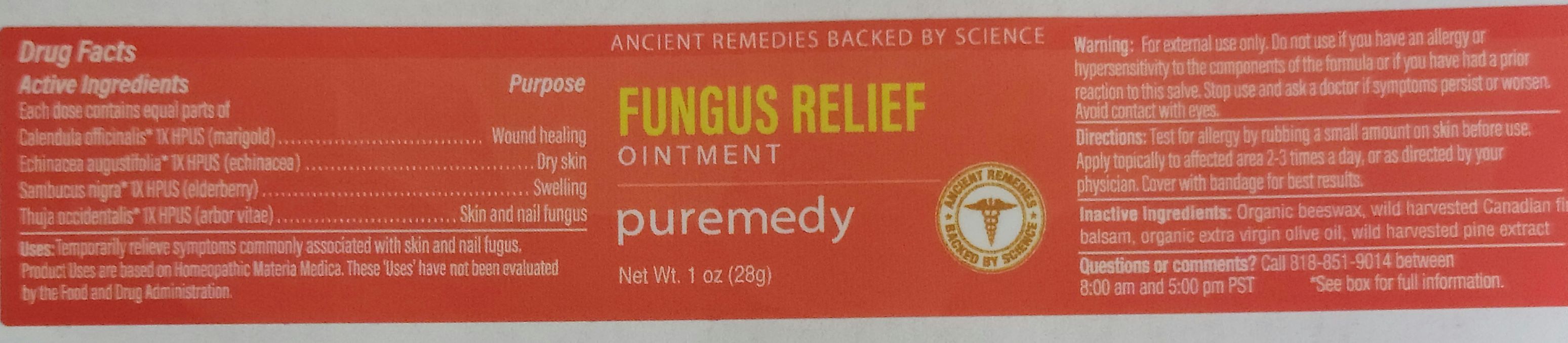 DRUG LABEL: FUNGUS FREE
NDC: 52810-511 | Form: SALVE
Manufacturer: PUREMEDY
Category: homeopathic | Type: HUMAN OTC DRUG LABEL
Date: 20240111

ACTIVE INGREDIENTS: SAMBUCUS NIGRA FLOWER 1 [hp_X]/100 mL; CALENDULA OFFICINALIS FLOWER 1 [hp_X]/100 mL; THUJA OCCIDENTALIS LEAFY TWIG 1 [hp_X]/100 mL; ECHINACEA ANGUSTIFOLIA 1 [hp_X]/100 mL
INACTIVE INGREDIENTS: OLIVE OIL; SAFFLOWER OIL; YELLOW WAX; CANADA BALSAM; PINE NEEDLE OIL (PINUS SYLVESTRIS); OREGANO LEAF OIL; TEA TREE OIL; AZADIRACHTA INDICA SEED OIL

FUNGUS FREE (52810-511)

ACTIVE INGREDIENTS

*SAMBUCUS NIGRA (1X) HPUS (ELDER FLOWER AND BARK)

*CALENDULA OFFIC. (1X) HPUS) (MARIGOLD)

*THUJA OCCIDENT. (1X) HPUS (WHITE CEDAR)

*ECHINACEA ANGUSTIFOLIA (1X)

PURPOSE

PROPERTIES

SKIN PROTECTANT

SKIN PROTECTANT

PROMOTES HEALTHY SKIN AND HEALING

FUNGUS TREATMENT FOR SKIN AND NAILS

INDICATIONS AND USAGE

USES: TO RELIEVE SYMPTOMS ASSOCIATED WITH SKIN AND NAIL FUNGUS. MAY BE USED GENITALLY.

DOSAGE AND ADMINISTRATION

DIRECTIONS: APPLY TO AFFECTED AREA 2-4 TIMES PER DAY.

INACTIVE INGREDIENT

OTHER INGREDIENTS: ORGANIC OLIVE OIL, SAFFLOWER OIL, ORGANIC BEESWAX, BALSAM FIR, ORGANIC OREGANO OIL, ORGANIC TEA TREE OIL, ORGANIC NEEM OIL.

WARNINGS

WARNING: TEST FOR ALLERGY BY RUBBING A SMALL AMOUNT ON SKIN FIRST. DO NOT USE IF ALLERGIC TO OR HYPER-SENSITIVE TO ANY INGREDIENT IN THIS SALVE. IF CONDITION PERSISTS OR WORSENS CONSULT YOUR HEALTH CARE PROVIDER. (* = CERTIFIED ORGANIC INGREDIENTS)

KEEP OUT OF REACH OF CHILDREN.

QUESTIONS

CUSTOMER SERVICE 310-526-6108

OTHER SAFETY INFORMATION

STORE IN A COOL DRY PLACE OR REFRIGERATE